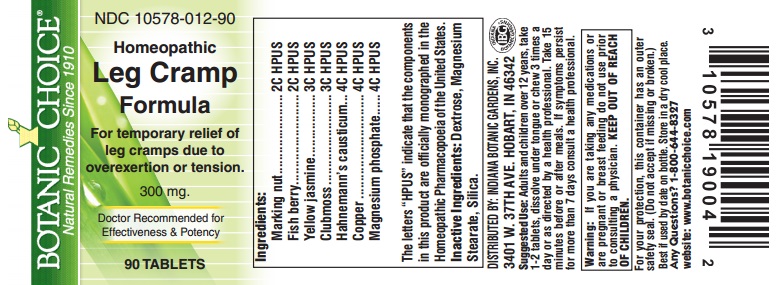 DRUG LABEL: Homeopathic Leg Cramp Formula
NDC: 10578-012 | Form: TABLET
Manufacturer: Indiana Botanic Gardens
Category: homeopathic | Type: HUMAN OTC DRUG LABEL
Date: 20150326

ACTIVE INGREDIENTS: SEMECARPUS ANACARDIUM JUICE 2 [hp_C]/1 1; ANAMIRTA COCCULUS SEED 2 [hp_C]/1 1; GELSEMIUM SEMPERVIRENS ROOT 3 [hp_C]/1 1; LYCOPODIUM CLAVATUM SPORE 3 [hp_C]/1 1; CAUSTICUM 4 [hp_C]/1 1; COPPER 4 [hp_C]/1 1; MAGNESIUM PHOSPHATE, DIBASIC TRIHYDRATE 4 [hp_C]/1 1
INACTIVE INGREDIENTS: DEXTROSE; MAGNESIUM STEARATE ; SILICON DIOXIDE 

Homeopathic Leg Cramp Formula

Ingredients:

Marking nut .......................2C HPUS

Fish berry..........................2C HPUS

Yellow jasmine ..................3C HPUS

Clubmoss ..........................3C HPUS

Hahnemann's causticum ...4C HPUS

Copper ..............................4C HPUS

Magnesium phosphate ......4C HPUS

The letters "HPUS" indicate that the components in this product are officially monographed in the

Homeopathic Pharmacopoeia of the United States.

Inactive Ingredients:

Dextrose, Magnesium Stearate, Silica.

DISTRIBUTED BY: INDIANA BOTANIC GARDENS, INC.

3401 W. 37TH AVE. HOBART, IN 46342

Suggested Use:

Adults and children over 12 years, take 1-2 tablets, dissolve under tongue or chew 3 times a day or as directed by a health professional. Take 15 minutes before or after meals.

STOP USE

If symptoms persist for more than 7 days consult a health professional.

Warning:

If you are taking any medications or are pregnant or breast feeding do not use prior to consulting a physician.

KEEP OUT OF REACH OF CHILDREN.

For your protection, this container has an outer safety seal. (Do not accept if missing or broken.)

Best if used by date on bottle. Store in a dry cool place.

Any Questions?

1-800-644-8327

website: www.botanicchoice.com

INDICATIONS AND USAGE

For temporary relief of leg cramps due to overexertion or tension.

PURPOSE

For temporary relief of leg cramps due to overexertion or tension.

Botanic Choice

Natural Remedies Since 1910

NDC 10578-012-90

Homeopathic Leg Cramp Formula

For temporary relief of leg cramps due to overexertion or tension.

300 mg.

Doctor Recommended for Effectiveness & Potency

90 TABLETS